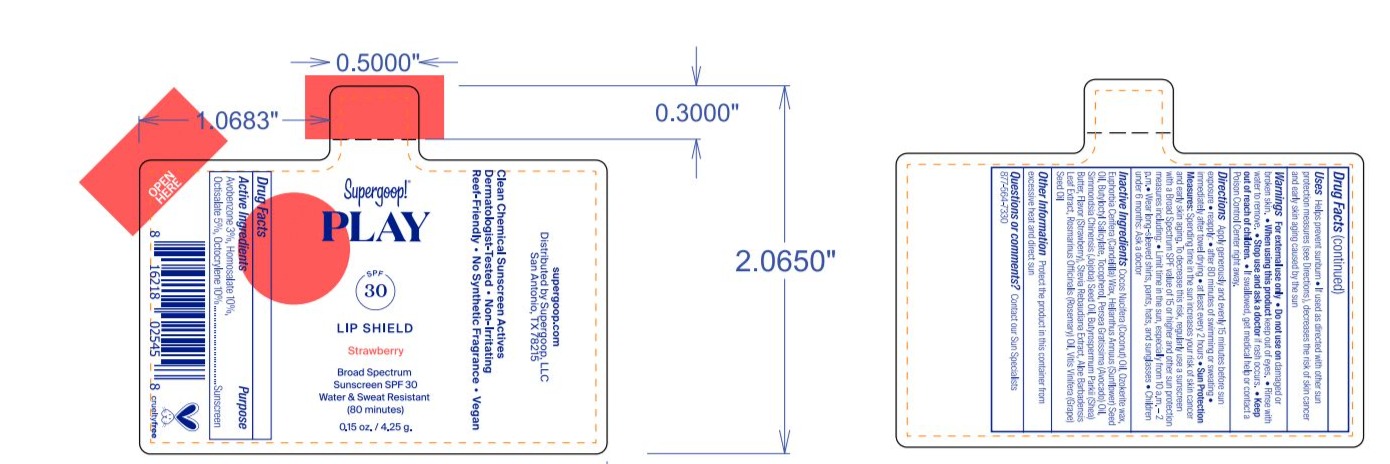 DRUG LABEL: Play SPF 30 Lip Shield Strawberry
NDC: 75936-155 | Form: GEL
Manufacturer: Supergoop, LLC
Category: otc | Type: HUMAN OTC DRUG LABEL
Date: 20231128

ACTIVE INGREDIENTS: OCTOCRYLENE 10 g/100 g; HOMOSALATE 10 g/100 g; AVOBENZONE 3 g/100 g; OCTISALATE 5 g/100 g
INACTIVE INGREDIENTS: STRAWBERRY; STEVIA REBAUDIANA WHOLE; SUNFLOWER OIL; ROSEMARY; ALOE VERA LEAF; GRAPE SEED OIL; TOCOPHEROL; BUTYLOCTYL SALICYLATE; SHEA BUTTER; COCONUT OIL; CANDELILLA WAX; CERESIN; AVOCADO OIL; JOJOBA OIL

Play SPF 30 Lip Shield Strawberry

ACTIVE INGREDIENT

Avobenzone 3%, Homosalate 10%, Octisalate 5%, Octocrylene 10%........ Purpose Suncreen

PURPOSE

Sunscreen

Keep out of reach of children.

If swallowed, get medical help or contact a Poison Control Center right away.

INDICATIONS AND USAGE

Helps prevent sunburn.

If used as directed with other sun protection measures (see Directions), decreases the risk of skin cancer and early skin aging caused by the sun.

Stop use and ask a doctor if rash occurs.

WARNINGS

For external use only.

Do not use on damaged or broken skin.

When using this product keep out of eyes. Rinse with water to remove.

Directions

Apply generously and evenly 15 minutes before sun exposure.

reapply:

- after 80 minutes of swimming or sweating.
- immediately after towel drying
- at least every 2 hours
- Sun Protection Measures: Spending time in the sun increases your risk of skin cancer and early sking aging. To decrease this risk, regularly use a sunscreen with a Broad Spectrum SPF value of 15 or higher and other sun protection measures including:
- Limit time in the sun, especially from 10 a.m. - 2 p.m.
- Wear long-sleeved shirts, pants, hats, and sunglasses
- Children under 6 months: Ask a doctor.

INACTIVE INGREDIENT

Butyloctyl Salicylate, Butyrospermum Parkii (Shea) Butter, Cocos Nucifera (Coconut) Oil, Euphorbia Cerifera (Candelila) Wax, Flavor (Strawberry), Aloe Barbadensis Leaf Extract, Helianthus Annuus (Sunflower) Seed Oil, Ozokerite Wax, Persea Gratissima (Avocado) Oil, Rosmarinus Officinalis (Rosemary) Leaf Extract, Simmondsia Chinensis (Jojoba) Seed Oil, Stevia Rebaudiana Extract, Tocopherol, Vitis Vinifera (Grape) Seed Oil

STORAGE AND HANDLING

Protect the product in this container from excessive heat and direct sun.

PACKAGE LABEL

Supergoop!

PLAY

SPF 30

LIP SHIELD

Strawberry

Borad Spectrum Sunscreen SPF 30

Water & Sweat Resistant

(80 minutes)

0.15 oz. / 4.25 g.